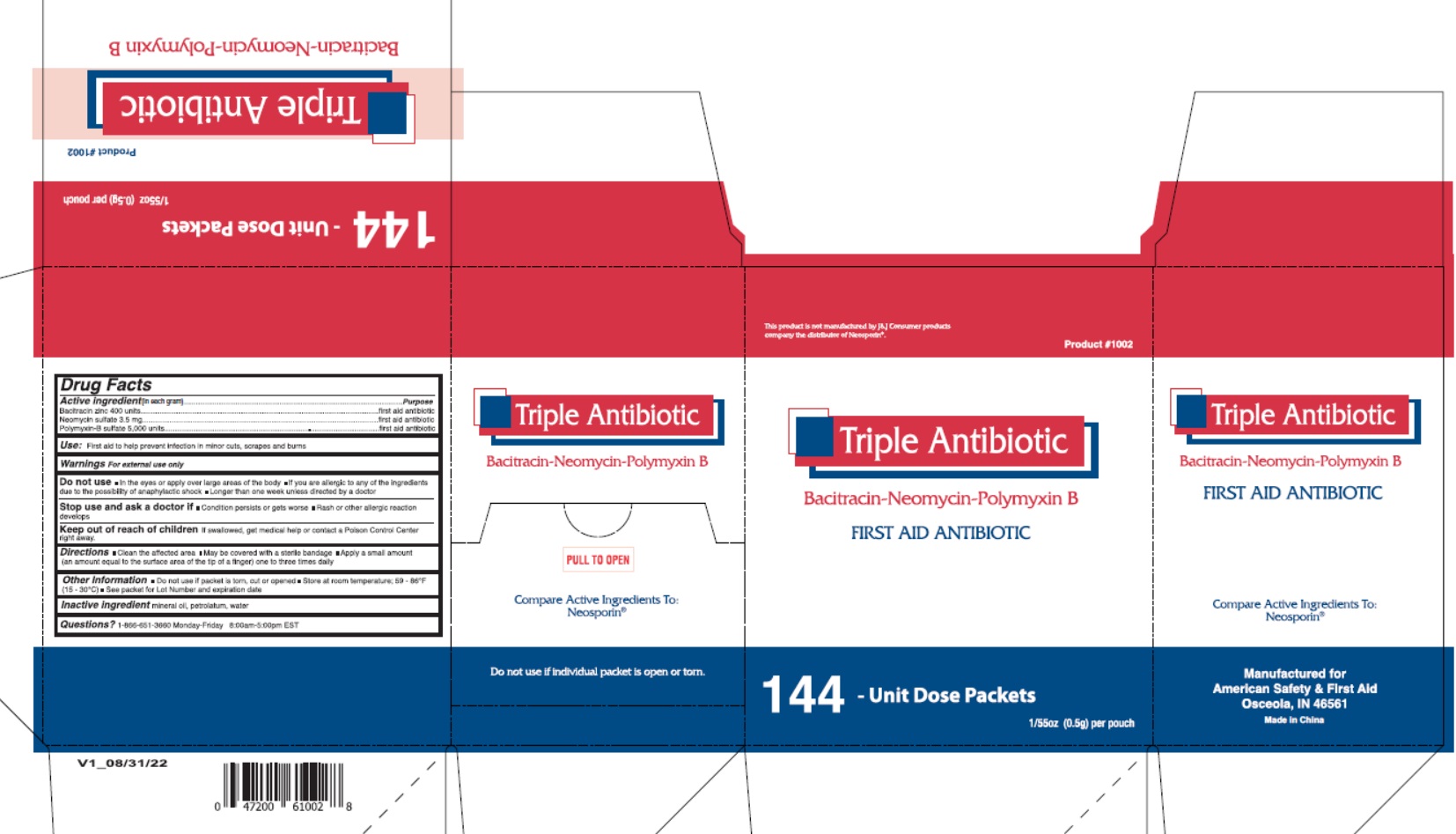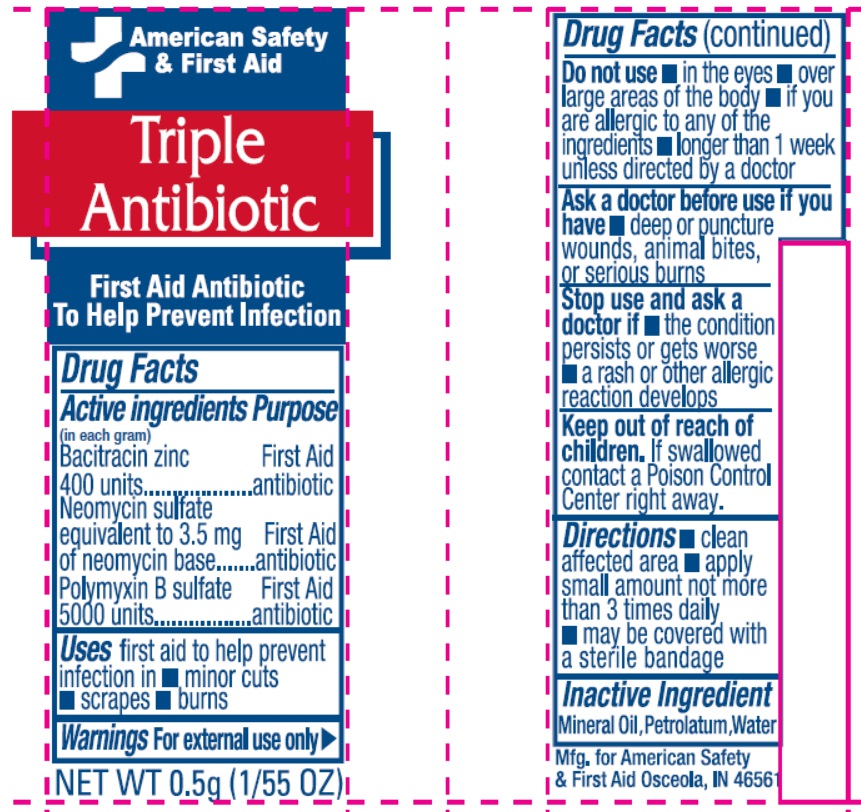 DRUG LABEL: American Safety and First Aid Triple Antibiotic
NDC: 71927-016 | Form: OINTMENT
Manufacturer: Orazen Inc
Category: otc | Type: HUMAN OTC DRUG LABEL
Date: 20240115

ACTIVE INGREDIENTS: BACITRACIN ZINC 400 [USP'U]/1 g; NEOMYCIN SULFATE 0.0035 g/1 g; POLYMYXIN B SULFATE 5000 [USP'U]/1 g
INACTIVE INGREDIENTS: MINERAL OIL; PETROLATUM; WATER

71927-016 American Safety & First Aid Triple Antibiotic

Active ingredients

(in each gram)

Bacitracin zinc 400 units

Neoycin sulfate equivalent to 3.5 mg of neomycin base

Polymyxin B sulfate 5,000 units

Purpose

First Aid antibiotic

First Aid antibiotic

First Aid antibiotic

Uses

first aid to help prevent infection in

- minor cuts
- scrapes
- burns

Warning

For external use only.

Do not use

- in eyes
- over large areas of the body
- if you are allergic to any of the ingredients
- longer than 1 week unless directed by a doctor

Ask a doctor before use if you have

deep or puncture wounds, animal bites, or serious burns

Stop use and ask a doctor if

- the condition persists or gets worse
- a rash or other allergic reaction develops

Keep out of reach of children.

If swallowed contact a Poison Control Center right away.

Directions

- clean affected area
- apply small amount not more than 3 times daily
- may be covered with a sterile bandage

Inactive Ingredient

Mineral Oil, Petrolatum, Water